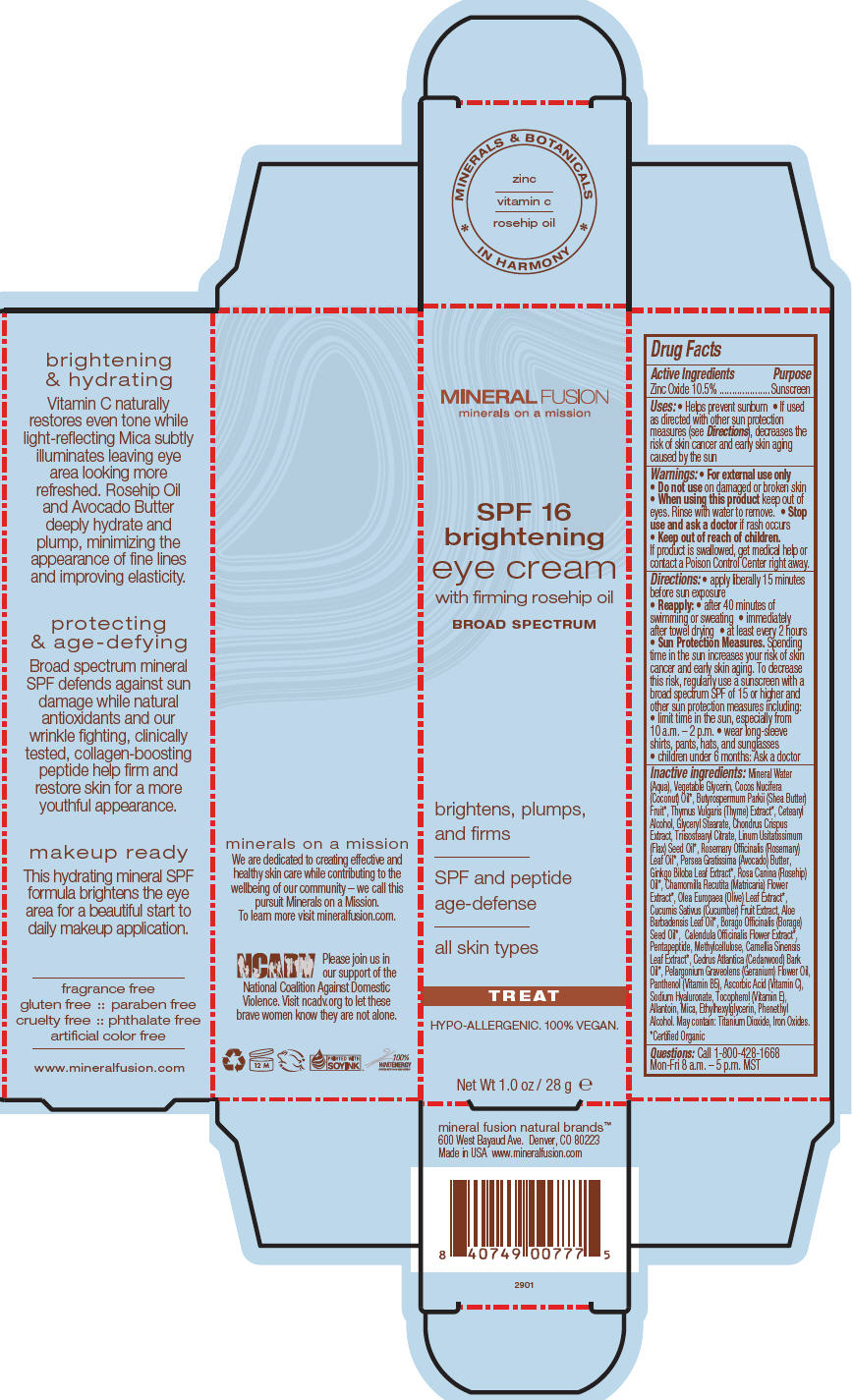 DRUG LABEL: SPF 16 BRIGHTENING
NDC: 55789-2901 | Form: CREAM
Manufacturer: Mineral Fusion Natural Brands
Category: otc | Type: HUMAN OTC DRUG LABEL
Date: 20150821

ACTIVE INGREDIENTS: ZINC OXIDE 2.94 g/28 g
INACTIVE INGREDIENTS: WATER 19.6 g/28 g; GLYCERIN; COCONUT OIL; SHEA BUTTER; THYME; CETOSTEARYL ALCOHOL; GLYCERYL MONOSTEARATE; CHONDRUS CRISPUS CARRAGEENAN; TRIISOSTEARYL CITRATE; LINSEED OIL; ROSEMARY OIL; AVOCADO SEED BUTTER; GINKGO; ROSA CANINA FLOWER OIL; CHAMOMILE; OLEA EUROPAEA LEAF; CUCUMBER; ALOE VERA LEAF; BORAGE OIL; CALENDULA OFFICINALIS FLOWER; METHYLCELLULOSE (400 MPA.S); GREEN TEA LEAF; CEDRUS ATLANTICA BARK OIL; PELARGONIUM GRAVEOLENS FLOWER OIL; PANTHENOL; ASCORBIC ACID; HYALURONATE SODIUM; TOCOPHEROL; ALLANTOIN; MICA; ETHYLHEXYLGLYCERIN; PHENYLETHYL ALCOHOL

SPF 16 BRIGHTENING CREAM

Drug Facts

Active Ingredients

Zinc Oxide 10.5%

Purpose

Sunscreen

Uses

- Helps prevent sunburn
- If used as directed with other sun protection measures (see Directions), decreases the risk of skin cancer and early skin aging caused by the sun

Warnings

- For external use only

- Do not use on damaged or broken skin

- When using this product keep out of eyes. Rinse with water to remove.

- Stop use and ask a doctor if rash occurs

- Keep out of reach of children.

If product is swallowed, get medical help or contact a Poison Control Center right away.

Directions

- apply liberally 15 minutes before sun exposure
- Reapply:
  - after 40 minutes of swimming or sweating
  - immediately after towel drying
  - at least every 2 hours
- Sun Protection Measures. Spending time in the sun increases your risk of skin cancer and early skin aging. To decrease this risk, regularly use a sunscreen with a broad spectrum SPF of 15 or higher and other sun protection measures including:
  - limit time in the sun, especially from 10 a.m. – 2 p.m.
  - wear long-sleeve shirts, pants, hats, and sunglasses
- children under 6 months: Ask a doctor

Inactive ingredients

Mineral Water (Aqua), Vegetable Glycerin, Cocos Nucifera (Coconut) Oil [Certified Organic] , Butyrospermum Parkii (Shea Butter) Fruit, Thymus Vulgaris (Thyme) Extract, Cetearyl Alcohol, Glyceryl Stearate, Chondrus Crispus Extract, Triisostearyl Citrate, Linum Usitatissimum (Flax) Seed Oil, Rosemary Officinalis (Rosemary) Leaf Oil, Persea Gratissima (Avocado) Butter, Ginkgo Biloba Leaf Extract, Rosa Canina (Rosehip) Oil, Chamomilla Recutita (Matricaria) Flower Extract, Olea Europaea (Olive) Leaf Extract, Cucumis Sativus (Cucumber) Fruit Extract, Aloe Barbadensis Leaf Oil, Borago Officinalis (Borage) Seed Oil, Calendula Officinalis Flower Extract, Pentapeptide, Methylcellulose, Camellia Sinensis Leaf Extract, Cedrus Atlantica (Cedarwood) Bark Oil, Pelargonium Graveolens (Geranium) Flower Oil, Panthenol (Vitamin B5), Ascorbic Acid (Vitamin C), Sodium Hyaluronate, Tocopherol (Vitamin E), Allantoin, Mica, Ethylhexylglycerin, Phenethyl Alcohol. May contain: Titanium Dioxide, Iron Oxides.

Questions

Call 1-800-428-1668
Mon-Fri 8 a.m. – 5 p.m. MST

PRINCIPAL DISPLAY PANEL - 28 g Tube Carton

MINERAL FUSION
minerals on a mission

SPF 16
brightening
eye cream
with firming rosehip oil
BROAD SPECTRUM

brightens, plumps,
and firms

SPF and peptide
age-defense

all skin types

TREAT

HYPO-ALLERGENIC. 100% VEGAN.

Net Wt 1.0 oz / 28 g e